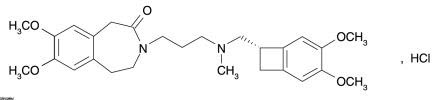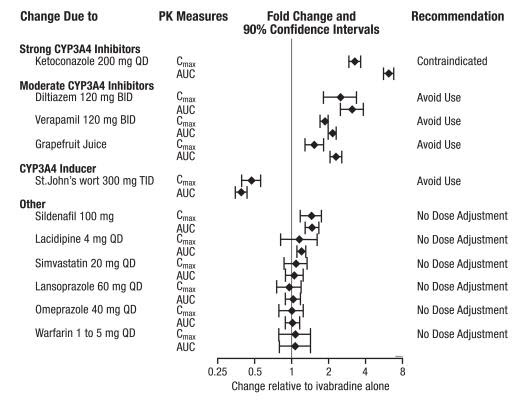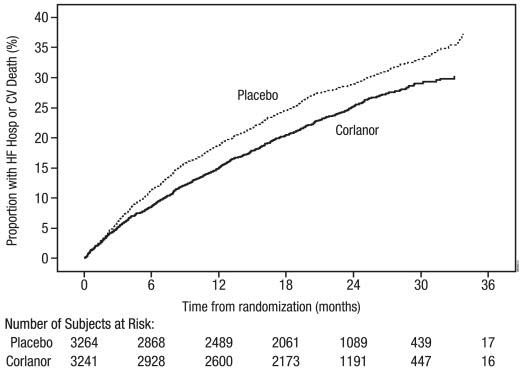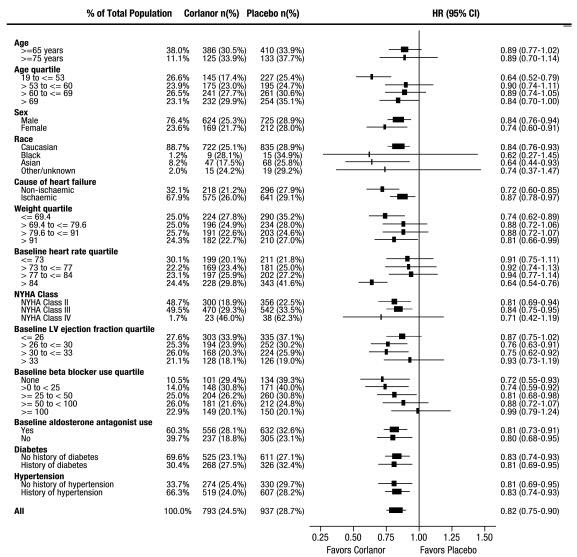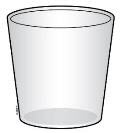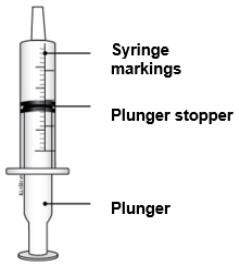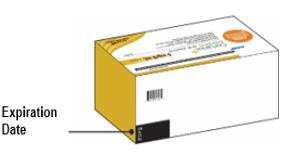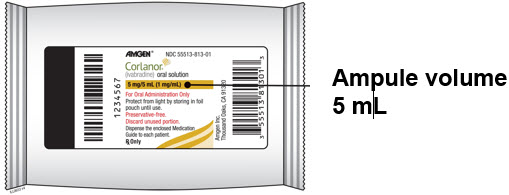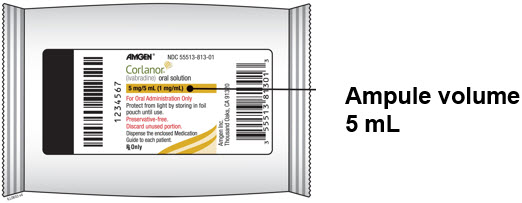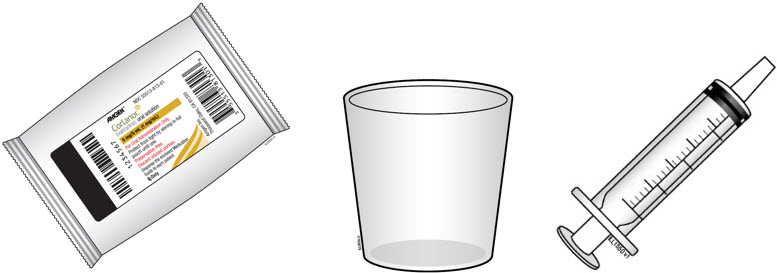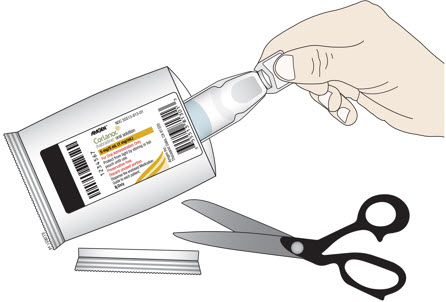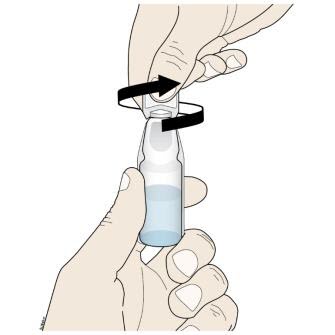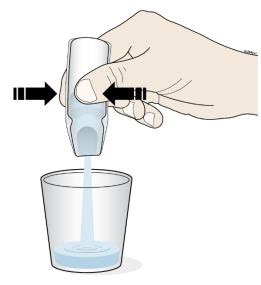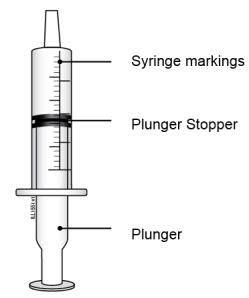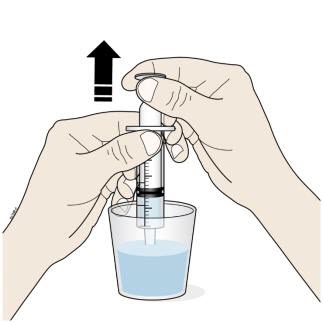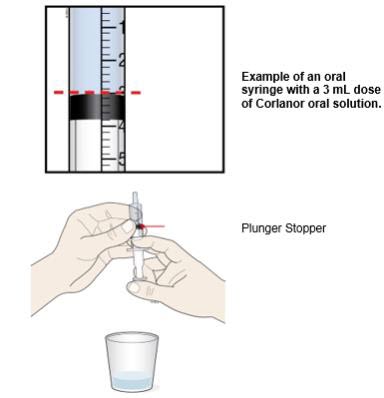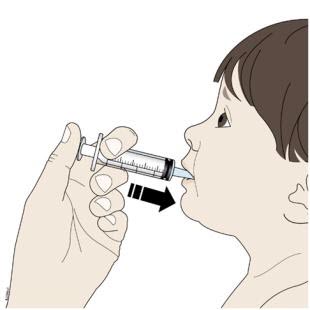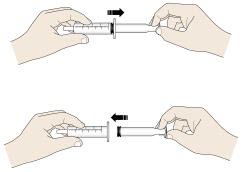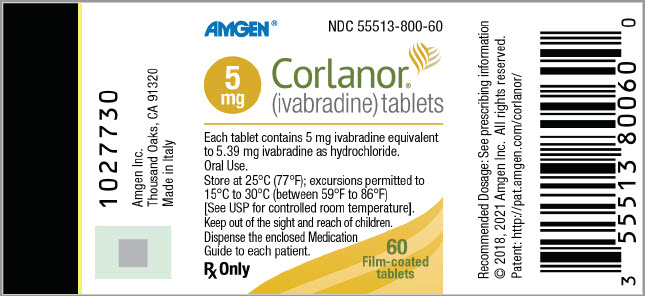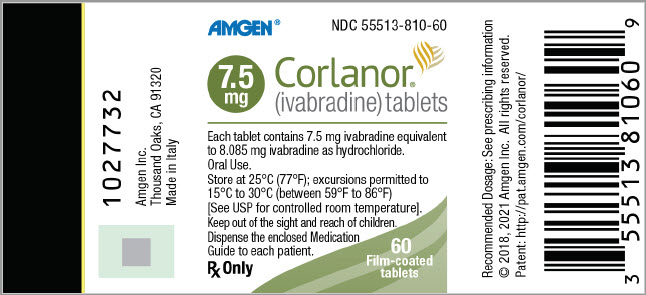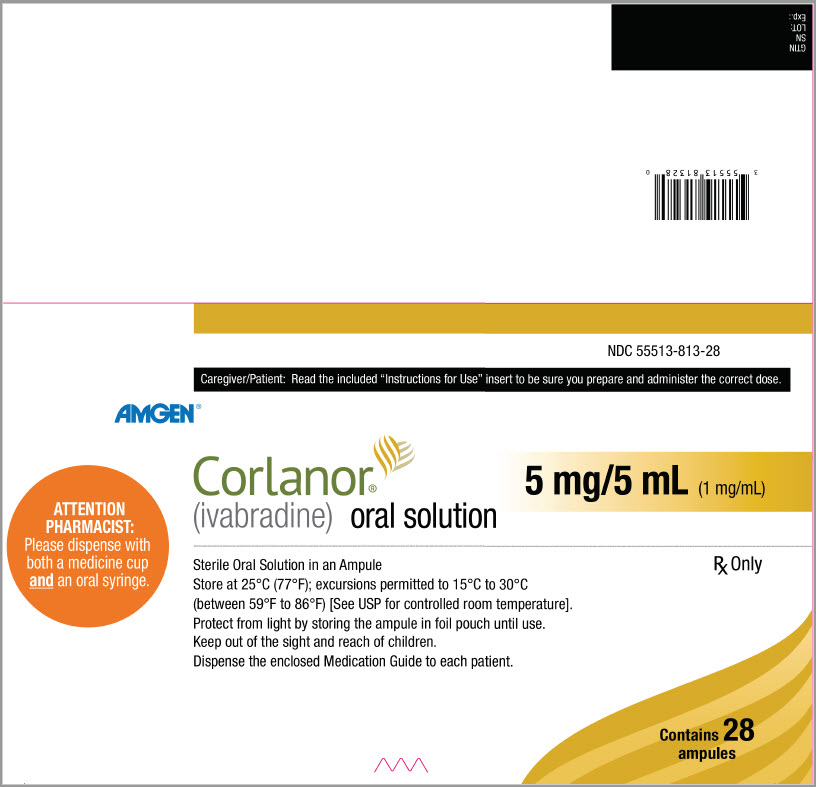 DRUG LABEL: Corlanor
NDC: 55513-800 | Form: TABLET, FILM COATED
Manufacturer: Amgen Inc
Category: prescription | Type: HUMAN PRESCRIPTION DRUG LABEL
Date: 20251110

ACTIVE INGREDIENTS: IVABRADINE HYDROCHLORIDE 5 mg/1 1
INACTIVE INGREDIENTS: LACTOSE MONOHYDRATE; STARCH, CORN; MALTODEXTRIN; MAGNESIUM STEARATE; SILICON DIOXIDE; HYPROMELLOSE, UNSPECIFIED; TITANIUM DIOXIDE; GLYCERIN; POLYETHYLENE GLYCOL 6000; FERRIC OXIDE YELLOW; FERRIC OXIDE RED

HIGHLIGHTS OF PRESCRIBING INFORMATION

These highlights do not include all the information needed to use CORLANOR safely and effectively. See full prescribing information for CORLANOR.
CORLANOR® (ivabradine) tablets, for oral use
CORLANOR® (ivabradine) oral solution
Initial U.S. Approval: 2015

1. INDICATIONS AND USAGE

Corlanor (ivabradine) is a hyperpolarization-activated cyclic nucleotide-gated channel blocker indicated:

- To reduce the risk of hospitalization for worsening heart failure in adult patients with stable, symptomatic chronic heart failure with reduced left ventricular ejection fraction. (1.1)
- For the treatment of stable symptomatic heart failure due to dilated cardiomyopathy in pediatric patients ages 6 months and older. (1.2)

2. DOSAGE AND ADMINISTRATION

Adult and pediatric patients greater than 40 kg

- Starting dose is 2.5 (pediatrics and vulnerable adults) or 5 mg twice daily with food. After 2 weeks of treatment, adjust dose based on heart rate. The maximum dose is 7.5 mg twice daily. (2.1)

Pediatric patients less than 40 kg

- Starting dose is 0.05 mg/kg twice daily with food. Adjust dose at two-week intervals by 0.05 mg/kg based on heart rate. Maximum dose is 0.2 mg/kg (patients 6 months to less than 1 year old) or 0.3 mg/kg (patients 1 year old and older), up to a total of 7.5 mg twice daily.

3. DOSAGE FORMS AND STRENGTHS

- Tablets: 5 mg, 7.5 mg (3)
- Oral Solution: 5 mg/5 mL (1 mg/mL) (3)

4. CONTRAINDICATIONS

- Acute decompensated heart failure (4)
- Clinically significant hypotension (4)
- Sick sinus syndrome, sinoatrial block or 3rd degree AV block, unless a functioning demand pacemaker is present (4)
- Clinically significant bradycardia (4)
- Severe hepatic impairment (4)
- Heart rate maintained exclusively by the pacemaker (4)
- In combination with strong cytochrome CYP3A4 inhibitors (4)

5. WARNINGS AND PRECAUTIONS

- Fetal toxicity: Females should use effective contraception. (5.1)
- Monitor patients for atrial fibrillation. (5.2)
- Monitor heart rate decreases and bradycardia symptoms during treatment. (5.3)
- Not recommended in patients with 2nd degree AV block. (5.3)

6. ADVERSE REACTIONS

Most common adverse reactions occurring in ≥ 1% of patients are bradycardia, hypertension, atrial fibrillation and luminous phenomena (phosphenes). (6)

To report SUSPECTED ADVERSE REACTIONS, contact Amgen Medical Information at 1-800-772-6436 (1-800-77-AMGEN) or FDA at 1-800-FDA-1088 or www.fda.gov/medwatch.

7. DRUG INTERACTIONS

- Avoid CYP3A4 inhibitors or inducers. (7.1)
- Negative chronotropes increase risk of bradycardia; monitor heart rate. (7.2)

8. USE IN SPECIFIC POPULATIONS

- Lactation: Breastfeeding not recommended. (8.2)

FULL PRESCRIBING INFORMATION

1. INDICATIONS AND USAGE

1.1 Heart Failure in Adult Patients

Corlanor is indicated to reduce the risk of hospitalization for worsening heart failure in adult patients with stable, symptomatic chronic heart failure with left ventricular ejection fraction ≤ 35%, who are in sinus rhythm with resting heart rate ≥ 70 beats per minute and either are on maximally tolerated doses of beta-blockers or have a contraindication to beta-blocker use.

1.2 Heart Failure in Pediatric Patients

Corlanor is indicated for the treatment of stable symptomatic heart failure due to dilated cardiomyopathy (DCM) in pediatric patients aged 6 months and older, who are in sinus rhythm with an elevated heart rate.

2. DOSAGE AND ADMINISTRATION

2.1 Adults

The recommended starting dose of Corlanor is 5 mg twice daily with food. Assess patient after two weeks and adjust dose to achieve a resting heart rate between 50 and 60 beats per minute (bpm) as shown in Table 1. Thereafter, adjust dose as needed based on resting heart rate and tolerability. The maximum dose is 7.5 mg twice daily. In adult patients unable to swallow tablets, Corlanor oral solution can be used [see Clinical Pharmacology (12.3)].

In patients with a history of conduction defects or other patients in whom bradycardia could lead to hemodynamic compromise, initiate therapy at 2.5 mg twice daily before increasing the dose based on heart rate [see Warnings and Precautions (5.3)].

Table 1. Dose Adjustment for Adults
Heart Rate | Dose Adjustment
> 60 bpm | Increase dose by 2.5 mg (given twice daily) up to a maximum dose of 7.5 mg twice daily
50-60 bpm | Maintain dose
< 50 bpm or signs and symptoms of bradycardia | Decrease dose by 2.5 mg (given twice daily); if current dose is 2.5 mg twice daily, discontinue therapy*

*[see Warnings and Precautions (5.3)]

2.2 Pediatric Patients

Recommended Dosage

Pediatric Patients 6 Months of Age and Older Weighing Less than 40 kg (Oral Solution)

The recommended starting dose of Corlanor oral solution in pediatric patients 6 months of age and older and weighing less than 40 kg is 0.05 mg/kg twice daily with food. Assess patient at two-week intervals and adjust dose by 0.05 mg/kg to target a heart rate (HR) reduction of at least 20%, based on tolerability. The maximum dose is 0.2 mg/kg twice daily for patients 6 months to less than 1 year old, and 0.3 mg/kg twice daily for patients 1 year old and older, up to a total of 7.5 mg twice daily.

If a dose of Corlanor is missed or spit out, do not give another dose to make up for the missed or spit out dose. Give the next dose at the usual time.

Pediatric Patients Weighing 40 kg and Greater (Tablets)

The recommended starting dose of Corlanor tablets in pediatric patients weighing more than 40 kg is 2.5 mg twice daily with food. Assess patient at two-week intervals and adjust dose by 2.5 mg to target a heart rate (HR) reduction of at least 20%, based on tolerability. The maximum dose is 7.5 mg twice daily. In patients unable to swallow tablets, Corlanor oral solution can be used.

Dose Reduction for Bradycardia

If bradycardia develops, reduce the dose to the previous titration step. In patients who develop bradycardia at the recommended initial dosage, consider reducing the dosage to 0.02 mg/kg twice daily.

Oral Solution Preparation and Administration

To administer Corlanor oral solution, empty the entire contents of the ampule(s) into a medication cup. With a calibrated oral syringe, measure the prescribed dose of Corlanor from the medication cup and administer the drug orally.

Corlanor oral solution is sterile and preservative-free. Discard the unused oral solution. Do not store or reuse any oral solution left in either the medication cup or an ampule.

3. DOSAGE FORMS AND STRENGTHS

Corlanor Tablets

5 mg: salmon-colored, oval-shaped, film-coated tablet, functionally scored on both edges, debossed with “5” on one face and bisected on the other face. The tablet is scored and can be divided into equal halves to provide a 2.5 mg dose.

7.5 mg: salmon-colored, triangular-shaped, film-coated tablet debossed with “7.5” on one face and plain on the other face.

Corlanor Oral Solution

Corlanor 5 mg/5 mL (1 mg/mL) oral solution is a colorless liquid in an opaque, plastic, ampule containing 5 mg of Corlanor in 5 mL of liquid.

4. CONTRAINDICATIONS

Corlanor is contraindicated in patients with:

• Acute decompensated heart failure

• Clinically significant hypotension

• Sick sinus syndrome, sinoatrial block or 3rd degree AV block, unless a functioning demand pacemaker is present

• Clinically significant bradycardia [see Warnings and Precautions (5.3)]

• Severe hepatic impairment [see Use in Specific Populations (8.6)]

• Pacemaker dependence (heart rate maintained exclusively by the pacemaker) [see Drug Interactions (7.3)]

• Concomitant use of strong cytochrome P450 3A4 (CYP3A4) inhibitors [see Drug Interactions (7.1)]

5. WARNINGS AND PRECAUTIONS

5.1 Fetal Toxicity

Corlanor may cause fetal toxicity when administered to a pregnant woman based on findings in animal studies. Embryo-fetal toxicity and cardiac teratogenic effects were observed in fetuses of pregnant rats treated during organogenesis at exposures 1 to 3 times the human exposures (AUC0-24hr) at the maximum recommended human dose (MRHD) [see Use in Specific Populations (8.1)]. Advise females of reproductive potential to use effective contraception when taking Corlanor [see Use in Specific Populations (8.3)].

5.2 Atrial Fibrillation

Corlanor increases the risk of atrial fibrillation. In the Systolic Heart Failure Treatment with the If Inhibitor Ivabradine Trial (SHIFT), the rate of atrial fibrillation was 5.0% per patient-year in patients treated with Corlanor and 3.9% per patient-year in patients treated with placebo [see Clinical Studies (14)]. Regularly monitor cardiac rhythm. Discontinue Corlanor if atrial fibrillation develops.

5.3 Bradycardia and Conduction Disturbances

Adult Patients

Bradycardia, sinus arrest, and heart block have occurred with Corlanor. The rate of bradycardia was 6.0% per patient-year in patients treated with Corlanor (2.7% symptomatic; 3.4% asymptomatic) and 1.3% per patient-year in patients treated with placebo. Risk factors for bradycardia include sinus node dysfunction, conduction defects (e.g., 1st or 2nd degree atrioventricular block, bundle branch block), ventricular dyssynchrony, and use of other negative chronotropes (e.g., digoxin, diltiazem, verapamil, amiodarone). Bradycardia may increase the risk of QT prolongation which may lead to severe ventricular arrhythmias, including torsade de pointes, especially in patients with risk factors such as use of QTc prolonging drugs [see Adverse Reactions (6.2)].

Concurrent use of verapamil or diltiazem will increase Corlanor exposure, may themselves contribute to heart rate lowering, and should be avoided [see Clinical Pharmacology (12.3)]. Avoid use of Corlanor in patients with 2nd degree atrioventricular block unless a functioning demand pacemaker is present [see Contraindications (4)].

Pediatric Patients
Bradycardia and first-degree heart block were observed in pediatric patients treated with Corlanor. Asymptomatic and symptomatic bradycardia were observed in 6.8% and 4.1% of pediatric patients treated with Corlanor, respectively. In the placebo treatment arm, 2.4% of pediatric patients had asymptomatic bradycardia, but none had symptomatic bradycardia. Bradycardia was managed through dose titration but did not result in study drug discontinuation [see Dosage and Administration (2.2)].

6. ADVERSE REACTIONS

Clinically significant adverse reactions that appear in other sections of the labeling include:

- Atrial Fibrillation [see Warnings and Precautions (5.2)]
- Bradycardia and Conduction Disturbances [see Warnings and Precautions (5.3)]

6.1 Clinical Trials Experience

Because clinical trials are conducted under widely varying conditions, adverse reaction rates observed in the clinical trials of a drug cannot be directly compared to rates in the clinical trials of another drug and may not reflect the rates observed in practice.

Adult Patients with Heart Failure

In SHIFT, safety was evaluated in 3,260 patients treated with Corlanor and 3,278 patients given placebo. The median duration of Corlanor exposure was 21.5 months.

The most common adverse drug reactions in the SHIFT trial are shown in Table 2 [see Warnings and Precautions (5.2), (5.3)].

Table 2. Adverse Drug Reactions with Rates ≥ 1.0% Higher on Ivabradine than Placebo occurring in > 1% on Ivabradine in SHIFT
 | Ivabradine N = 3,260 | Placebo N = 3,278
Bradycardia | 10% | 2.2%
Hypertension, blood pressure increased | 8.9% | 7.8%
Atrial fibrillation | 8.3% | 6.6%
Phosphenes, visual brightness | 2.8% | 0.5%

Luminous Phenomena (Phosphenes)

Phosphenes are phenomena described as a transiently enhanced brightness in a limited area of the visual field, halos, image decomposition (stroboscopic or kaleidoscopic effects), colored bright lights, or multiple images (retinal persistency). Phosphenes are usually triggered by sudden variations in light intensity. Corlanor can cause phosphenes, thought to be mediated through Corlanor’s effects on retinal photoreceptors [see Clinical Pharmacology (12.1)]. Onset is generally within the first 2 months of treatment, after which they may occur repeatedly. Phosphenes were generally reported to be of mild to moderate intensity and led to treatment discontinuation in < 1% of patients; most resolved during or after treatment.

Pediatric Patients with Heart Failure

The safety of Corlanor in pediatric patients 6 months to less than 18 years of age is based on a clinical trial [see Clinical Studies (14.2)] in symptomatic heart failure patients with dilated cardiomyopathy and elevated heart rate. This trial provides experience in 73 patients treated with Corlanor for a median duration of 397 days, and 42 patients given placebo. Bradycardia (symptomatic and asymptomatic) occurred at rates similar to those in adults. Phosphenes were observed in pediatric patients treated with Corlanor.

6.2 Postmarketing Experience

Because these reactions are reported voluntarily from a population of uncertain size, it is not always possible to estimate their frequency reliably or establish a causal relationship to drug exposure.

The following adverse reactions have been identified in adults during post-approval use of Corlanor: syncope, hypotension, torsade de pointes, ventricular fibrillation, ventricular tachycardia, angioedema, erythema, rash, pruritus, urticaria, vertigo, and diplopia, and visual impairment.

7. DRUG INTERACTIONS

7.1 Cytochrome P450-Based Interactions

Corlanor is primarily metabolized by CYP3A4. Concomitant use of CYP3A4 inhibitors increases ivabradine plasma concentrations and use of CYP3A4 inducers decreases them. Increased plasma concentrations may exacerbate bradycardia and conduction disturbances.

The concomitant use of strong CYP3A4 inhibitors is contraindicated [see Contraindications (4) and Clinical Pharmacology (12.3)]. Examples of strong CYP3A4 inhibitors include azole antifungals (e.g., itraconazole), macrolide antibiotics (e.g., clarithromycin, telithromycin), HIV protease inhibitors (e.g., nelfinavir), and nefazodone.

Avoid concomitant use of moderate CYP3A4 inhibitors when using Corlanor. Examples of moderate CYP3A4 inhibitors include diltiazem, verapamil, and grapefruit juice [see Warnings and Precautions (5.3) and Clinical Pharmacology (12.3)].

Avoid concomitant use of CYP3A4 inducers when using Corlanor. Examples of CYP3A4 inducers include St. John’s wort, rifampicin, barbiturates, and phenytoin [see Clinical Pharmacology (12.3)].

7.2 Negative Chronotropes

Most patients receiving Corlanor will also be treated with a beta-blocker. The risk of bradycardia increases with concomitant administration of drugs that slow heart rate (e.g., digoxin, amiodarone, beta-blockers). Monitor heart rate in patients taking Corlanor with other negative chronotropes.

7.3 Pacemakers in Adults

Corlanor dosing is based on heart rate reduction, targeting a heart rate of 50 to 60 beats per minute in adults [see Dosage and Administration (2.1)]. Patients with demand pacemakers set to a rate ≥ 60 beats per minute cannot achieve a target heart rate < 60 beats per minute, and these patients were excluded from clinical trials [see Clinical Studies (14.1)]. The use of Corlanor is not recommended in patients with demand pacemakers set to rates ≥ 60 beats per minute.

8. USE IN SPECIFIC POPULATIONS

8.1 Pregnancy

Risk Summary

Based on findings in animals, Corlanor may cause fetal harm when administered to a pregnant woman. There are no adequate and well-controlled studies of Corlanor in pregnant women to inform any drug-associated risks. In animal reproduction studies, oral administration of ivabradine to pregnant rats during organogenesis at a dosage providing 1 to 3 times the human exposure (AUC0-24hr) at the MRHD resulted in embryo-fetal toxicity and teratogenicity manifested as abnormal shape of the heart, interventricular septal defect, and complex anomalies of primary arteries. Increased post-natal mortality was associated with these teratogenic effects in rats. In pregnant rabbits, increased post-implantation loss was noted at an exposure (AUC0-24hr) 5 times the human exposure at the MRHD. Lower doses were not tested in rabbits. The background risk of major birth defects for the indicated population is unknown. The estimated background risk of major birth defects in the U.S. general population is 2 to 4%, however, and the estimated risk of miscarriage is 15 to 20% in clinically recognized pregnancies. Advise a pregnant woman of the potential risk to the fetus.

Clinical Considerations

Disease-associated Maternal and/or Embryo-fetal Risk

Stroke volume and heart rate increase during pregnancy, increasing cardiac output, especially during the first trimester. Pregnant patients with left ventricular ejection fraction less than 35% on maximally tolerated doses of beta-blockers may be particularly heart rate dependent for augmenting cardiac output. Therefore, pregnant patients who are started on Corlanor, especially during the first trimester, should be followed closely for destabilization of their congestive heart failure that could result from heart rate slowing.

Monitor pregnant women with chronic heart failure in 3rd trimester of pregnancy for preterm birth.

Data

Animal Data

In pregnant rats, oral administration of ivabradine during the period of organogenesis (gestation day 6-15) at doses of 2.3, 4.6, 9.3, or 19 mg/kg/day resulted in fetal toxicity and teratogenic effects. Increased intrauterine and post-natal mortality and cardiac malformations were observed at doses ≥ 2.3 mg/kg/day (equivalent to the human exposure at the MRHD based on AUC0-24hr). Teratogenic effects including interventricular septal defect and complex anomalies of major arteries were observed at doses ≥ 4.6 mg/kg/day (approximately 3 times the human exposure at the MRHD based on AUC0-24hr).

In pregnant rabbits, oral administration of ivabradine during the period of organogenesis (gestation day 6-18) at doses of 7, 14, or 28 mg/kg/day resulted in fetal toxicity and teratogenicity. Treatment with all doses ≥ 7 mg/kg/day (equivalent to the human exposure at the MRHD based on AUC0-24hr) caused an increase in post-implantation loss. At the high dose of 28 mg/kg/day (approximately 15 times the human exposure at the MRHD based on AUC0-24hr), reduced fetal and placental weights were observed, and evidence of teratogenicity (ectrodactylia observed in 2 of 148 fetuses from 2 of 18 litters) was demonstrated.

In the pre- and post-natal study, pregnant rats received oral administration of ivabradine at doses of 2.5, 7, or 20 mg/kg/day from gestation day 6 to lactation day 20. Increased post-natal mortality associated with cardiac teratogenic findings was observed in the F1 pups delivered by dams treated at the high dose (approximately 15 times the human exposure at the MRHD based on AUC0-24hr).

8.2 Lactation

Risk Summary

There is no information regarding the presence of ivabradine in human milk, the effects of ivabradine on the breastfed infant, or the effects of the drug on milk production. Animal studies have shown, however, that ivabradine is present in rat milk [see Data]. Because of the potential risk to breastfed infants from exposure to Corlanor, breastfeeding is not recommended.

Data

Lactating rats received daily oral doses of [14C]-ivabradine (7 mg/kg) on post-parturition days 10 to 14; milk and maternal plasma were collected at 0.5 and 2.5 hours post-dose on day 14. The ratios of total radioactivity associated with [14C]-ivabradine or its metabolites in milk vs. plasma were 1.5 and 1.8, respectively, indicating that ivabradine is transferred to milk after oral administration.

8.3 Females and Males of Reproductive Potential

Contraception

Females

Corlanor may cause fetal harm, based on animal data. Advise females of reproductive potential to use effective contraception during Corlanor treatment [see Use in Specific Populations (8.1)].

8.4 Pediatric Use

The safety and effectiveness of Corlanor have been established in pediatric patients (age 6 months to less than 18 years old) and are supported by pharmacokinetic and pharmacodynamic trials and evidence from adequate and well-controlled trials of Corlanor in adult patients. The pediatric study included 116 patients in the following age groups: 17 patients in the 6 months to less than 12 months age group, 36 patients in the 1 year to less than 3 years age group, and 63 patients in the 3 years to less than 18 years age group [see Dosage and Administration (2.2), Adverse Reactions (6.1), Clinical Pharmacology (12.3) and Clinical Studies (14.2)].

The safety and efficacy of Corlanor have not been established in patients less than 6 months of age.

Animal Data

Ivabradine given orally to juvenile rats from post-natal day (PND) 7 until PND 77 at 7.5, 15 and 30 mg/kg/day did not affect post-natal (pre-weaning) development and reproductive performance (post-weaning development). Similar to adult animals, ivabradine decreased heart rate dose-dependently, and increased heart weights at the highest dose administered. Ivabradine also decreased white blood cell counts (lymphocytes) at the highest dose administered. The decrease in white blood cell counts partially reversed within a 3-week recovery period. Exposures in male and female rats at the No Observed Adverse Effect Level (NOAEL) of 7.5 mg/kg/day, was approximately 3 and 8 times, respectively, steady state exposure associated with the highest received maintenance doses across age groups in pediatric patients (based on AUCs).

8.5 Geriatric Use

No pharmacokinetic differences have been observed in elderly (≥ 65 years) or very elderly (≥ 75 years) patients compared to the overall population. However, Corlanor has only been studied in a limited number of patients ≥ 75 years of age.

8.6 Hepatic Impairment

No dose adjustment is required in patients with mild or moderate hepatic impairment. Corlanor is contraindicated in patients with severe hepatic impairment (Child-Pugh C) as it has not been studied in this population and an increase in systemic exposure is anticipated [see Contraindications (4) and Clinical Pharmacology (12.3)].

8.7 Renal Impairment

No dosage adjustment is required for patients with creatinine clearance 15 to 60 mL/min. No data are available for patients with creatinine clearance below 15 mL/min [see Clinical Pharmacology (12.3)].

10. OVERDOSAGE

Overdose may lead to severe and prolonged bradycardia. In the event of bradycardia with poor hemodynamic tolerance, temporary cardiac pacing may be required. Supportive treatment, including intravenous (IV) fluids, atropine, and intravenous beta-stimulating agents such as isoproterenol, may be considered.

11. DESCRIPTION

Corlanor (ivabradine) tablets and oral solution contains ivabradine as the active pharmaceutical ingredient. Ivabradine is a hyperpolarization-activated cyclic nucleotide-gated channel blocker that reduces the spontaneous pacemaker activity of the cardiac sinus node by selectively inhibiting the If current, resulting in heart rate reduction with no effect on ventricular repolarization and no effects on myocardial contractility.

The chemical name for ivabradine hydrochloride is 3-(3-{[((7S)-3,4-Dimethoxybicyclo[4.2.0]octa-1,3,5-trien-7-yl)methyl] methyl amino} propyl)-1,3,4,5-tetrahydro-7,8-dimethoxy-2H-3-benzazepin-2-one, hydrochloride. The molecular formula is C27H36N2O5∙HCl, and the molecular weight (free base + HCl) is 505.1 (468.6 + 36.5). The chemical structure of ivabradine is shown in Figure 1.

Figure 1. Chemical Structure of Ivabradine

Tablets

Corlanor tablets are supplied in 5 mg and 7.5 mg tablets for oral administration. The tablets contain 5 mg and 7.5 mg of ivabradine, as the active ingredient, equivalent to 5.39 mg and 8.09 mg of ivabradine hydrochloride, respectively. The tablets contain the following inactive ingredients: colloidal silicon dioxide, glycerol, hypromellose, lactose monohydrate, magnesium stearate, maize starch, maltodextrin, polyethylene glycol 6000, red iron oxide, titanium dioxide, and yellow iron oxide.

Oral Solution

Corlanor 5 mg/5 mL (1 mg/mL) oral solution is formulated as a sterile, preservative-free, colorless solution for oral administration. Each 5 mL ampule contains 5 mg of ivabradine, equivalent to 5.39 mg ivabradine hydrochloride, as the active ingredient. The solution contains the following inactive ingredients: maltitol and water.

12. CLINICAL PHARMACOLOGY

12.1 Mechanism of Action

Corlanor blocks the hyperpolarization-activated cyclic nucleotide-gated (HCN) channel responsible for the cardiac pacemaker If current, which regulates heart rate. In clinical electrophysiology studies, the cardiac effects were most pronounced in the sinoatrial (SA) node, but prolongation of the AH interval has occurred as has PR interval prolongation. There was no effect on ventricular repolarization and no effects on myocardial contractility [see Clinical Pharmacology (12.2)].

Corlanor can also inhibit the retinal current Ih. Ih is involved in curtailing retinal responses to bright light stimuli. Under triggering circumstances (e.g., rapid changes in luminosity), partial inhibition of Ih by Corlanor may underlie the luminous phenomena experienced by patients. Luminous phenomena (phosphenes) are described as a transient enhanced brightness in a limited area of the visual field [see Adverse Reactions (6.1)].

12.2 Pharmacodynamics

Corlanor causes a dose-dependent reduction in heart rate. The size of the effect is dependent on the baseline heart rate (i.e., greater heart rate reduction occurs in patients with higher baseline heart rate). At recommended doses, heart rate reduction is approximately 10 bpm at rest and during exercise. Analysis of heart rate reduction vs. dose indicates a plateau effect at doses > 20 mg twice daily. In a study of patients with preexisting conduction system disease (first- or second-degree AV block or left or right bundle branch block) requiring electrophysiologic study, IV ivabradine (0.20 mg/kg) administration slowed the overall heart rate by approximately 15 bpm, increased the PR interval (29 msec), and increased the AH interval (27 msec).

Corlanor does not have negative inotropic effects. Ivabradine increases the uncorrected QT interval with heart rate slowing but does not cause rate-corrected prolongation of QT.

12.3 Pharmacokinetics

The peak concentration (Cmax) and area under the plasma concentration time curve (AUC) are similar for ivabradine and S 18982 between oral solution and tablets for the same dose.

Absorption and Bioavailability

Following oral administration, peak plasma ivabradine concentrations are reached in approximately 1 hour under fasting conditions. The absolute oral bioavailability of ivabradine is approximately 40% because of first-pass elimination in the gut and liver.

Food delays absorption by approximately 1 hour and increases plasma exposure by 20% to 40%. Corlanor should be taken with food [see Dosage and Administration (2)].

Ivabradine is approximately 70% plasma protein bound, and the volume of distribution at steady state is approximately 100 L.

Metabolism and Excretion

The pharmacokinetics of ivabradine are linear over an oral dose range of 0.5 mg to 24 mg. Ivabradine is extensively metabolized in the liver and intestines by CYP3A4-mediated oxidation. The major metabolite is the N-desmethylated derivative (S 18982), which is equipotent to ivabradine and circulates at concentrations approximately 40% that of ivabradine. The N-desmethylated derivative is also metabolized by CYP3A4. Ivabradine plasma levels decline with a distribution half-life of 2 hours and an effective half-life of approximately 6 hours.

The total clearance of ivabradine is 24 L/h, and renal clearance is approximately 4.2 L/h, with ~ 4% of an oral dose excreted unchanged in urine. The excretion of metabolites occurs to a similar extent via feces and urine.

Drug Interactions

The effects of coadministered drugs (CYP3A4 inhibitors, substrates, inducers, and other concomitantly administered drugs) on the pharmacokinetics of Corlanor were studied in several single- and multiple-dose studies. Pharmacokinetic measures indicating the magnitude of these interactions are presented in Figure 2.

Figure 2. Impact of Coadministered Drugs on the Pharmacokinetics of Corlanor

Digoxin exposure did not change when concomitantly administered with ivabradine. No dose adjustment is required when ivabradine is concomitantly administered with digoxin.

Effect of Ivabradine on Metformin Pharmacokinetics

Ivabradine, dosed at 10 mg twice daily to steady state, did not affect the pharmacokinetics of metformin (an organic cation transporter [OCT2] sensitive substrate). The geometric mean (90% confidence interval [CI]) ratios of Cmax and AUCinf of metformin, with and without ivabradine were 0.98 [0.83–1.15] and 1.02 [0.86–1.22], respectively. No dose adjustment is required for metformin when administered with Corlanor.

Specific Populations

Age

No pharmacokinetic differences (AUC or Cmax) have been observed between elderly (≥ 65 years) or very elderly (≥ 75 years) patients and the overall patient population [see Use in Specific Populations (8.5)].

Hepatic Impairment

In patients with mild (Child-Pugh A) and moderate (Child-Pugh B) hepatic impairment, the pharmacokinetics of Corlanor were similar to that in patients with normal hepatic function. No data are available in patients with severe hepatic impairment (Child-Pugh C) [see Contraindications (4)].

Renal Impairment

Renal impairment (creatinine clearance from 15 to 60 mL/min) has minimal effect on the pharmacokinetics of Corlanor. No data are available for patients with creatinine clearance below 15 mL/min.

Pediatrics

The pharmacokinetics of ivabradine and the major metabolite S 18982 were evaluated in 70 pediatric patients with dilated cardiomyopathy and symptomatic chronic heart failure aged from 6 months to less than 18 years of age given ivabradine twice daily [see Clinical Studies (14.2)]. Ivabradine and S 18982 metabolite exposures were measured following weight-based dosing and dose titration designed to reach a dose that enables a 20% heart rate reduction without inducing bradycardia and/or signs or symptoms related to bradycardia. Analyses showed the relationship between exposure and heart rate reduction was similar across pediatric age groups and adults. Steady state exposures of ivabradine and S 18982 following maintenance doses in pediatric patients are similar to exposures achieved in adult heart failure patients given 5 mg BID.

13. NONCLINICAL TOXICOLOGY

13.1 Carcinogenesis, Mutagenesis, Impairment of Fertility

There was no evidence of carcinogenicity when mice and rats received ivabradine up to 104 weeks by dietary administration. High doses in these studies were associated with mean ivabradine exposures of at least 37 times higher than the human exposure (AUC0-24hr) at the MRHD.

Ivabradine tested negative in the following assays: bacterial reverse mutation (Ames) assay, in vivo bone marrow micronucleus assay in both mouse and rat, in vivo chromosomal aberration assay in rats, and in vivo unscheduled DNA synthesis assay in rats. Results of the in vitro chromosomal aberration assay were equivocal at concentrations approximately 1,500 times the human Cmax at the MRHD. Ivabradine tested positive in the mouse lymphoma assays and in vitro unscheduled DNA synthesis assay in rat hepatocytes at concentrations greater than 1,500 times the human Cmax at the MRHD.

Reproduction toxicity studies in animals demonstrated that ivabradine did not affect fertility in male or female rats at exposures 46 to 133 times the human exposure (AUC0-24hr) at the MRHD.

13.2 Animal Toxicology and/or Pharmacology

Reversible changes in retinal function were observed in dogs administered oral ivabradine at total doses of 2, 7, or 24 mg/kg/day (approximately 0.6 to 50 times the human exposure at the MRHD based on AUC0-24hr) for 52 weeks. Retinal function assessed by electroretinography demonstrated reductions in cone system responses, which reversed within a week post-dosing, and were not associated with damage to ocular structures as evaluated by light microscopy. These data are consistent with the pharmacological effect of ivabradine related to its interaction with hyperpolarization-activated Ih currents in the retina, which share homology with the cardiac pacemaker If current.

14. CLINICAL STUDIES

14.1 Heart Failure in Adult Patients

SHIFT

The Systolic Heart Failure Treatment with the If Inhibitor Ivabradine Trial (SHIFT) was a randomized, double-blind trial comparing Corlanor and placebo in 6,558 adult patients with stable New York Heart Association (NYHA) class II to IV heart failure, left ventricular ejection fraction ≤ 35%, and resting heart rate ≥ 70 bpm. Patients had to have been clinically stable for at least 4 weeks on an optimized and stable clinical regimen, which included maximally tolerated doses of beta-blockers and, in most cases, ACE inhibitors or ARBs, spironolactone, and diuretics, with fluid retention and symptoms of congestion minimized. Patients had to have been hospitalized for heart failure within 12 months prior to study entry.

The underlying cause of CHF was coronary artery disease in 68% of patients. At baseline, approximately 49% of randomized patients were NYHA class II, 50% were NYHA class III, and 2% were NYHA class IV. The mean left ventricular ejection fraction was 29%. All patients were initiated on Corlanor 5 mg (or matching placebo) twice daily and the dose was increased to 7.5 mg twice daily or decreased to 2.5 mg twice daily to maintain the resting heart rate between 50 and 60 bpm, as tolerated. The primary endpoint was a composite of the first occurrence of either hospitalization for worsening heart failure or cardiovascular death.

Most patients (89%) were taking beta-blockers, with 26% on guideline-defined target daily doses. The main reasons for not receiving the target beta-blocker doses at baseline were hypotension (45% of patients not at target), fatigue (32%), dyspnea (14%), dizziness (12%), history of cardiac decompensation (9%), and bradycardia (6%). For the 11% of patients not receiving any beta-blocker at baseline, the main reasons were chronic obstructive pulmonary disease, hypotension, and asthma. Most patients were also taking ACE inhibitors and/or angiotensin II antagonists (91%), diuretics (83%), and anti-aldosterone agents (60%). Few patients had an implantable cardioverter-defibrillator (ICD) (3.2%) or a cardiac resynchronization therapy (CRT) device (1.1%). Median follow-up was 22.9 months. At 1 month, 63%, 26%, and 8% of Corlanor-treated patients were taking 7.5, 5, and 2.5 mg BID, whereas 3% had withdrawn from the drug, primarily for bradycardia.

SHIFT demonstrated that Corlanor reduced the risk of the combined endpoint of hospitalization for worsening heart failure or cardiovascular death based on a time-to-event analysis (hazard ratio: 0.82, 95% confidence interval [CI]: 0.75, 0.90, p < 0.0001) (Table 3). The treatment effect reflected only a reduction in the risk of hospitalization for worsening heart failure; there was no favorable effect on the mortality component of the primary endpoint. In the overall treatment population, Corlanor had no statistically significant benefit on cardiovascular death.

Table 3. SHIFT – Incidence of the Primary Composite Endpoint and Components
 | Corlanor (N = 3,241) |  |  | Placebo (N = 3,264)
Endpoint | n | % | % PY | n | % | % PY | Hazard Ratio | [95% CI] | p-value
Primary composite endpoint: Time to first hospitalization for worsening heart failure or cardiovascular deatha | 793 | 24.5 | 14.5 | 937 | 28.7 | 17.7 | 0.82 | [0.75, 0.90] | < 0.0001
Hospitalization for worsening heart failure | 505 | 15.6 | 9.2 | 660 | 20.2 | 12.5
Cardiovascular death as first event | 288 | 8.9 | 4.8 | 277 | 8.5 | 4.7
Patients with events at any time
Hospitalization for worsening heart failureb | 514 | 15.9 | 9.4 | 672 | 20.6 | 12.7 | 0.74 | [0.66, 0.83]
Cardiovascular deathb | 449 | 13.9 | 7.5 | 491 | 15.0 | 8.3 | 0.91 | [0.80, 1.03]
a Patients who died on the same calendar day as their first hospitalization for worsening heart failure are counted under cardiovascular death.
b Analyses of the components of the primary composite endpoint were not prospectively planned to be adjusted for multiplicity.
N: number of patients at risk; n: number of patients having experienced the endpoint; %: incidence rate = (n/N) × 100; % PY: annual incidence rate = (n/number of patient-years) × 100; CI: confidence interval
The hazard ratio between treatment groups (ivabradine/placebo) was estimated based on an adjusted Cox proportional hazards model with beta-blocker intake at randomization (yes/no) as a covariate; p-value: Wald test

The Kaplan-Meier curve (Figure 3) shows time to first occurrence of the primary composite endpoint of hospitalization for worsening heart failure or cardiovascular death in the overall study.

Figure 3. SHIFT: Time to First Event of Primary Composite Endpoint

A wide range of demographic characteristics, baseline disease characteristics, and baseline concomitant medications were examined for their influence on outcomes. Many of these results are shown in Figure 4. Such analyses must be interpreted cautiously, as differences can reflect the play of chance among a large number of analyses.

Most of the results show effects consistent with the overall study result. Corlanor’s benefit on the primary endpoint in SHIFT appeared to decrease as the dose of beta-blockers increased, with little if any benefit demonstrated in patients taking guideline-defined target doses of beta-blockers.

Figure 4. Effect of Treatment on Primary Composite Endpoint in Subgroups

Note: The figure above presents effects in various subgroups, all of which are baseline characteristics. The 95% confidence limits that are shown do not take into account the number of comparisons made and may not reflect the effect of a particular factor after adjustment for all other factors. Apparent homogeneity or heterogeneity among groups should not be over-interpreted.

BEAUTIFUL and SIGNIFY: No benefit in stable coronary artery disease with or without stable heart failure

The Morbidity-mortality Evaluation of the If Inhibitor Ivabradine in Patients with Coronary Disease and Left Ventricular Dysfunction Trial (BEAUTIFUL) was a randomized, double-blind, placebo-controlled trial in 10,917 adult patients with coronary artery disease, impaired left ventricular systolic function (ejection fraction < 40%) and resting heart rate ≥ 60 bpm. Patients had stable symptoms of heart failure and/or angina for at least 3 months and were receiving conventional cardiovascular medications at stable doses for at least 1 month. Beta-blocker therapy was not required, nor was there a protocol mandate to achieve any specific dosing targets for patients who were taking beta-blockers. Patients were randomized 1:1 to Corlanor or placebo at an initial dose of 5 mg twice daily with the dose increased to 7.5 mg twice daily depending on resting heart rate and tolerability. The primary endpoint was the composite of time to first cardiovascular death, hospitalization for acute myocardial infarction, or hospitalization for new-onset or worsening heart failure. Most patients were NYHA class II (61.4%) or class III (23.2%) - none were class IV. Through a median follow-up of 19 months, Corlanor did not significantly affect the primary composite endpoint (HR 1.00, 95% CI = 0.91, 1.10).

The Study Assessing the Morbi-mortality Benefits of the If Inhibitor Ivabradine in Patients with Coronary Artery Disease Trial (SIGNIFY) was a randomized, double-blind trial administering Corlanor or placebo to 19,102 adult patients with stable coronary artery disease but without clinically evident heart failure (NYHA class I). Beta-blocker therapy was not required. Corlanor was initiated at a dose of 7.5 mg twice daily and the dose could be increased to as high as 10 mg twice daily or down-titrated to 5.0 mg twice daily to achieve a target heart rate of 55 to 60 bpm. The primary endpoint was a composite of the first occurrence of either cardiovascular death or myocardial infarction. Through a median follow-up of 24.1 months, Corlanor did not significantly affect the primary composite endpoint (HR 1.08, 95% CI = 0.96, 1.20).

14.2 Heart Failure in Pediatric Patients

Because Corlanor was effective in improving outcomes in patients with dilated cardiomyopathy (DCM) in SHIFT, the effect on heart rate was considered a reasonable basis to infer clinical benefits in pediatric patients with DCM. Thus, Corlanor was evaluated for its effect on heart rate in a multi-center, randomized, double-blind, placebo-controlled trial in children with symptomatic DCM. The study collected data from 116 patients aged 6 months to less than 18 years with DCM in sinus rhythm, NYHA/Ross class II to IV heart failure, and left ventricular ejection fraction ≤ 45%. Patients had to be clinically stable for at least 4 weeks and on optimized medical therapy with a resting heart rate (HR) complying with the following criteria:

- HR ≥ 105 bpm in the age-subset 6–12 months.
- HR ≥ 95 bpm in the age-subset 1–3 years.
- HR ≥ 75 bpm in the age-subset 3–5 years.
- HR ≥ 70 bpm in the age-subset 5–18 years.

Patients were randomized in a 2:1 ratio to receive Corlanor or placebo. Doses of study medication were titrated over a 2- to 8-week period to achieve a 20% heart rate reduction without inducing bradycardia. The target heart rate reduction was obtained at the end of the titration period in a significantly higher proportion of patients with Corlanor vs. placebo (72% vs. 16% respectively; Odds Ratio = 15; 95% CI = [5; 47]). A statistically significant reduction in HR was observed with Corlanor compared to placebo at the end of the titration period (-23 ± 11 bpm vs. -2 ± 12 bpm respectively).

16. HOW SUPPLIED/STORAGE AND HANDLING

Tablets:

Corlanor (ivabradine) 5 mg tablets are formulated as salmon-colored, oval-shaped, film-coated tablets functionally scored on both edges, marked with “5” on one face and bisected on the other face. They are supplied as follows:

- Bottles of 60 tablets with child-resistant closure (NDC 55513-800-60)

Corlanor (ivabradine) 7.5 mg tablets are formulated as salmon-colored, triangular-shaped, film-coated tablets debossed with “7.5” on one face and plain on the other face. They are supplied as follows:

- Bottles of 60 tablets with child-resistant closure (NDC 55513-810-60)

Oral Solution:

Corlanor (ivabradine) oral solution is a colorless liquid supplied in an opaque, low density polyethylene (LDPE) plastic ampule. Each 5 mL ampule is individually packaged in a child-resistant foil pouch and supplied in cartons containing 28 foil pouches. Corlanor oral solution is supplied as 5 mg/5 mL (1 mg/mL) (NDC 55513-813-01).

Storage

Store Corlanor tablets and oral solution at 25°C (77°F); excursions permitted to 15°C - 30°C (59°F - 86°F) [see USP Controlled Room Temperature]. Protect Corlanor ampule from light by storing in the foil pouch until use.

17. PATIENT COUNSELING INFORMATION

Advise the patient to read the FDA-approved patient labeling [see Medication Guide and Instructions for Use].

- Fetal Toxicity
  Advise pregnant women of the potential risks to a fetus.
  Advise females of reproductive potential to use effective contraception and to notify their healthcare provider with a known or suspected pregnancy [see Warnings and Precautions (5.1) and Use in Specific Populations (8.1), (8.3)].
- Low Heart Rate
  Advise patients to report significant decreases in heart rate or symptoms such as dizziness, fatigue, or hypotension [see Warnings and Precautions (5.3)].
- Atrial Fibrillation
  Advise patients to report symptoms of atrial fibrillation, such as heart palpitations or racing, chest pressure, or worsened shortness of breath [see Warnings and Precautions (5.2)].
- Phosphenes
  Advise patients about the possible occurrence of luminous phenomena (phosphenes). Advise patients to use caution if they are driving or using machines in situations where sudden changes in light intensity may occur, especially when driving at night. Advise patients that phosphenes may subside spontaneously during continued treatment with Corlanor [see Adverse Reactions (6.1)].
- Drug Interactions
  Advise patients to avoid ingestion of grapefruit juice and St. John’s wort [see Drug Interactions (7.1)].
- Intake with Food
  Advise patients to take Corlanor twice daily with food [see Dosage and Administration (2)].
- Oral Solution
  Advise parents/caregivers on preparation and administration instructions including the use of a calibrated oral syringe and a medicine cup (provided by the pharmacy) to avoid dosing errors [see Dosage and Administration (2.2)].
  Advise parents/caregivers that the oral solution should not be administered by the child.
  Advise parents/caregivers to not double up doses (e.g., if patient spits out the drug or caregiver forgets to give the drug at the prescribed time).
  Advise parents/caregivers to throw away the unused product remaining in the cup immediately after drawing up the prescribed dose in the syringe.

Corlanor® (ivabradine)

Manufactured by:
Amgen Inc.
One Amgen Center Drive
Thousand Oaks, California 91320-1799

Patent: http://pat.amgen.com/Corlanor/

© 2015, 2017, 2019, 2021 Amgen Inc. All rights reserved.
[part number] v5

MEDICATION GUIDE
Corlanor® (core lan ore)
(ivabradine)
tablets and oral solution

What is the most important information I should know about Corlanor?
Corlanor may cause serious side effects in adults and children, including:

- Harm to an unborn baby. Females who are able to get pregnant:
  ○ Must use effective birth control during treatment with Corlanor.
  ○ Tell your doctor right away if you become pregnant during treatment with Corlanor.
- Increased risk of irregular or rapid heartbeat (atrial fibrillation or heart rhythm problems). Tell your doctor if you feel any of the following symptoms of an irregular or rapid heartbeat:
  ○ heart is pounding or racing (palpitations).
  ○ chest pressure.
  ○ worsened shortness of breath.
  ○ near fainting or fainting.
- Slower than normal heart rate (bradycardia). Tell your doctor if you have:
  ○ a slowing of heart rate, or
  ○ symptoms of a slow heart rate such as dizziness, fatigue, lack of energy. In young children signs and symptoms of slow heart rate may include: poor feeding, difficulty breathing or turning blue.

What is Corlanor?
Corlanor is a prescription medicine used:

- to treat adults who have chronic (lasting a long time) heart failure, with symptoms, to reduce their risk of hospitalization for worsening heart failure.
- to treat certain children 6 months of age and older who have stable heart failure, with symptoms, that is due to an enlarged heart (dilated cardiomyopathy).

Who should not take Corlanor?
Do not take Corlanor if you have:

- symptoms of heart failure that recently worsened
- very low blood pressure (hypotension)
- certain heart conditions: sick sinus syndrome, sinoatrial block, or 3rd degree atrioventricular block
- a slow resting heart rate before treatment with Corlanor. Ask your doctor what a slow resting heart rate is for you.
- certain liver problems
- been prescribed any medicines that can increase the effects of Corlanor.

Ask your doctor if you are not sure if you have any of the medical conditions listed above.

What should I tell my doctor before taking Corlanor?
Before you take Corlanor, tell your doctor about all of your medical conditions, including if you:

- have any other heart problems, including heart rhythm problems, a slow heart rate, or a heart conduction problem.
- are breastfeeding or planning to breastfeed. It is not known if Corlanor passes into breast milk. You and your doctor should decide if you will take Corlanor or breastfeed; do not do both.
- are pregnant or planning to become pregnant. See “What is the most important information I should know about Corlanor? - Harm to an unborn baby” section.

Tell your doctor about all the medicines you take, including prescription and over the counter medicines, vitamins, and herbal supplements. Corlanor may affect the way other medicines work, and other medicines may affect how Corlanor works. This could cause serious side effects.

How should you take Corlanor?

- Take Corlanor exactly as your doctor tells you.
- Do not stop taking Corlanor without talking with your doctor.
- Corlanor comes as a tablet or as an oral solution.
  ○ Tell your doctor if you have trouble swallowing tablets.
  ○ Your doctor may change your dose of Corlanor during treatment
- If you are prescribed Corlanor oral solution, see the Instructions for Use that comes with your medicine for important information about how to prepare, and give or take a dose of Corlanor oral solution.
- Take Corlanor 2 times each day with food.
- If you miss a dose of Corlanor, do not give another dose. Give the next dose at the usual time.
- If you or your child take too much Corlanor, call your doctor or go to the nearest emergency room right away.

What should you avoid while taking Corlanor?

- Avoid drinking grapefruit juice and taking St. John’s wort during treatment with Corlanor. These can affect the way Corlanor works and may cause serious side effects.

What are the possible side effects of Corlanor?
Corlanor may cause serious side effects. See “What is the most important information I should know about Corlanor?”
The most common side effects of Corlanor are:

- increased blood pressure
- temporary brightness in part of your field of vision. This is usually caused by sudden changes in light (luminous phenomena). This brightness usually happens within the first 2 months of treatment with Corlanor and may go away during or after treatment with Corlanor. Be careful when driving or operating machinery where sudden changes in light can happen, especially when driving at night.

These are not all the side effects of Corlanor. Ask your doctor or pharmacist for more information.
Call your doctor for medical advice about side effects. You may report side effects to FDA at 1-800-FDA-1088.

How should I store Corlanor?

- Store Corlanor at room temperature between 68°F to 77°F (20°C to 25°C).
- Keep Corlanor ampules in the unopened child-resistant foil pouch until ready to use, to protect from light.
- Do not save or reuse any leftover Corlanor oral solution. Corlanor oral solution is sterile and does not contain a preservative.

Keep Corlanor and all medicines out of the reach of children.

General information about the safe and effective use of Corlanor.
Medicines are sometimes prescribed for purposes other than those listed in a Medication Guide. Do not use Corlanor for a condition for which it was not prescribed. Do not give Corlanor to other people, even if they have the same symptoms that you have. It may harm them. You can ask your doctor or pharmacist for information about Corlanor that is written for health professionals.

What are the ingredients in Corlanor?
Active ingredient: ivabradine
Inactive ingredients:
Tablet: colloidal silicon dioxide, glycerol, hypromellose, lactose monohydrate, magnesium stearate, maize starch, maltodextrin, polyethylene glycol 6000, red iron oxide, titanium dioxide, yellow iron oxide
Oral Solution: Maltitol and water
Manufactured by: Amgen Inc. One Amgen Center Drive Thousand Oaks, California 91320 1799
Patent: http://pat.amgen.com/Corlanor/
© 2015, 2017, 2019, 2021 Amgen Inc. All rights reserved.
[part number] v5
For more information, go to www.Corlanor.com or call 1-800-772-6436.

This Medication Guide has been approved by the U.S. Food and Drug Administration.
Revised: August 2021

Instructions for Use
Corlanor® (core lan ore) (ivabradine)
oral solution
Ampule

Important

Before you use Corlanor oral solution, read this important information.
Using

- These instructions are for use by adults who are preparing and taking Corlanor or giving Corlanor to an adult or child who cannot swallow tablets.
- When you receive your Corlanor oral solution carton, always check to see that the name “Corlanor” is on it and that the expiration date on the carton has not passed. Do not use an ampule of Corlanor after the expiration date on the carton.
- Corlanor oral solution comes in an ampule that contains 5 mL of medicine.
- The dose may be higher or lower than 1 ampule. To prepare a dose, you may need to use only part of an ampule or more than 1 ampule of Corlanor.
- Corlanor should only be given by an adult. A child should not give or take a dose of Corlanor by themselves.

Storing

- Store Corlanor oral solution at room temperature between 68°F to 77°F (20°C to 25°C).
- Keep Corlanor oral solution ampules in their unopened child-resistant foil pouch until ready to use, to protect from light.
- Keep Corlanor and all medicines out of the reach of children.
- Throw away any unused Corlanor oral solution right away after measuring the dose using the oral syringe. Do not save or reuse any leftover Corlanor oral solution. Corlanor oral solution does not contain a preservative.

Measuring

- Your pharmacist should provide you with an oral syringe to measure and give the prescribed dose. Always use the oral syringe given to you by your pharmacist to measure the prescribed dose. Call your pharmacist if you have not been given an oral syringe.
- If you have any questions, ask your or your child’s healthcare provider or pharmacist to show you how to measure and give the prescribed dose of Corlanor oral solution.

For more information or help, go to www.Corlanor.com or call 1-800-722-6436.

Supplies needed to take or give a dose of Corlanor

From the pharmacist

1 reusable medicine cup
Measure the dose with the oral syringe. Do not measure the dose with the medicine cup.
Do not throw away the medicine cup.

1 reusable oral syringe
Oral syringes come in different sizes
(Example: 0.5 mL, 1 mL, 3 mL, 5 mL, 10 mL).
Your pharmacist will give you the correct syringe depending on the dose.
If you do not receive an oral syringe and medicine cup from your pharmacist, or if you have any questions about your oral syringe, call your healthcare provider or pharmacist.
Do not throw away the oral syringe unless you can no longer clearly see the markings. If you are not sure what to do, ask your healthcare provider or pharmacist.

The carton

The carton contains 28 ampules in individual foil pouches.

Each foil pouch contains 1 ampule of Corlanor oral solution.

Step 1: Prepare

A. Check your prescription.

- If the prescribed dose is 5 mL or less, you will use 1 ampule pouch. If the prescribed dose is more than 5 mL, you will use 2 ampule pouches.
- Once you have opened an ampule, do not save unused Corlanor oral solution for later use.

B. Gather the supplies you will need.

- 1 or 2 Corlanor oral solution foil pouches
- 1 oral syringe (provided by the pharmacist)
- 1 medicine cup (provided by the pharmacist)

C. Cut open the foil pouch and remove the ampule. Be careful not to cut the ampule inside. Repeat with another foil pouch if you need more than 1 ampule for the prescribed dose.

Step 2: Empty

D. To open the ampule, twist the plastic top in either direction.

- Turn the ampule(s) upside down and squeeze to empty all of the Corlanor oral solution into the medicine cup.
- Repeat Step D if more than 1 ampule of Corlanor is needed for a prescribed dose.

Important:

- Throw away the ampules and plastic tops in household trash.

Step 3: Check

E. Check the dose in milliliters (mL) prescribed by your healthcare provider.
Then find that number on the oral syringe. Your syringe and dose may look different from the example shown here.

Step 4: Measure

F. Insert the tip of the oral syringe into the oral solution and slowly pull up on the plunger until the plunger stopper lines up with the syringe marking for the prescribed dose.

- Do not pull the plunger all the way out.
- Avoid pulling bubbles into the oral syringe.

G. Turn the oral syringe right side up. Hold the syringe over the medicine cup to catch any Corlanor that might drip.
H. Adjust the amount of the Corlanor oral solution in the syringe if needed to match your prescribed dose:

- Gently press up on the plunger until the top edge of the plunger stopper lines up with the mL marking on the syringe that matches the prescribed dose.
- If you see air bubbles in the oral syringe, empty the oral solution back into the medicine cup. Repeat Steps F through H.

Step 5: Give

I. Place the tip of the oral syringe into your or your child’s mouth and towards the cheek.
Then slowly push down on the plunger until the oral syringe is empty.

Important:
If you miss a dose of Corlanor, do not give another dose. Give the next dose at the usual time.

Step 6: Finish

J. Rinse the reusable oral syringe and reusable medicine cup for the next dose.

- Remove the plunger from the oral syringe. Rinse the inside and outside of the oral syringe and the plunger well, with warm running water.
- Rinse the medicine cup with warm, running water.
- Place the clean oral syringe parts and medicine cup on a clean paper towel to dry.
- After the syringe parts and medicine cup dry, put the oral syringe together so that it is ready for the next use.

This Instructions for Use has been approved by the U.S. Food and Drug Administration.

Manufactured by:

Amgen Inc.

Thousand Oaks, California 91320-1799

Patent: http://pat/amgen.com/Corlanor/

© 2019, 2021 Amgen Inc. All rights reserved.

[partnumber] v2

Issued: 08/2021

PRINCIPAL DISPLAY PANEL - 5 mg Tablet Bottle Label

AMGEN®

NDC 55513-800-60

5
mg

Corlanor®
(ivabradine) tablets

Each tablet contains 5 mg ivabradine equivalent
to 5.39 mg ivabradine as hydrochloride.
Oral Use.
Store at 25°C (77°F); excursions permitted to
15°C to 30°C (between 59°F to 86°F)
[See USP for controlled room temperature].
Keep out of the sight and reach of children.
Dispense the enclosed Medication
Guide to each patient.

Rx Only

60
Film-coated
tablets

PRINCIPAL DISPLAY PANEL - 7.5 mg Tablet Bottle Label

AMGEN®

NDC 55513-810-60

7.5
mg

Corlanor®
(ivabradine) tablets

Each tablet contains 7.5 mg ivabradine equivalent
to 8.085 mg ivabradine as hydrochloride.
Oral Use.
Store at 25°C (77°F); excursions permitted to
15°C to 30°C (between 59°F to 86°F)
[See USP for controlled room temperature].
Keep out of the sight and reach of children.
Dispense the enclosed Medication
Guide to each patient.

Rx Only

60
Film-coated
tablets

PRINCIPAL DISPLAY PANEL - 5 mg/5 mL Ampule Carton

NDC 55513-813-28

Caregiver/Patient: Read the included "Instructions for Use" insert to be sure you prepare and administer the correct dose.

AMGEN®

ATTENTION
PHARMACIST:
Please dispense with
both a medicine cup
and an oral syringe.

Corlanor®
(ivabradine) oral solution

5 mg/5 mL (1 mg/mL)

Sterile Oral Solution in an Ampule
Store at 25°C (77°F); excursions permitted to 15°C to 30°C
(between 59°F to 86°F) [See USP for controlled room temperature].
Protect from light by storing the ampule in foil pouch until use.
Keep out of the sight and reach of children.
Dispense the enclosed Medication Guide to each patient.

Rx Only

Contains 28
ampules